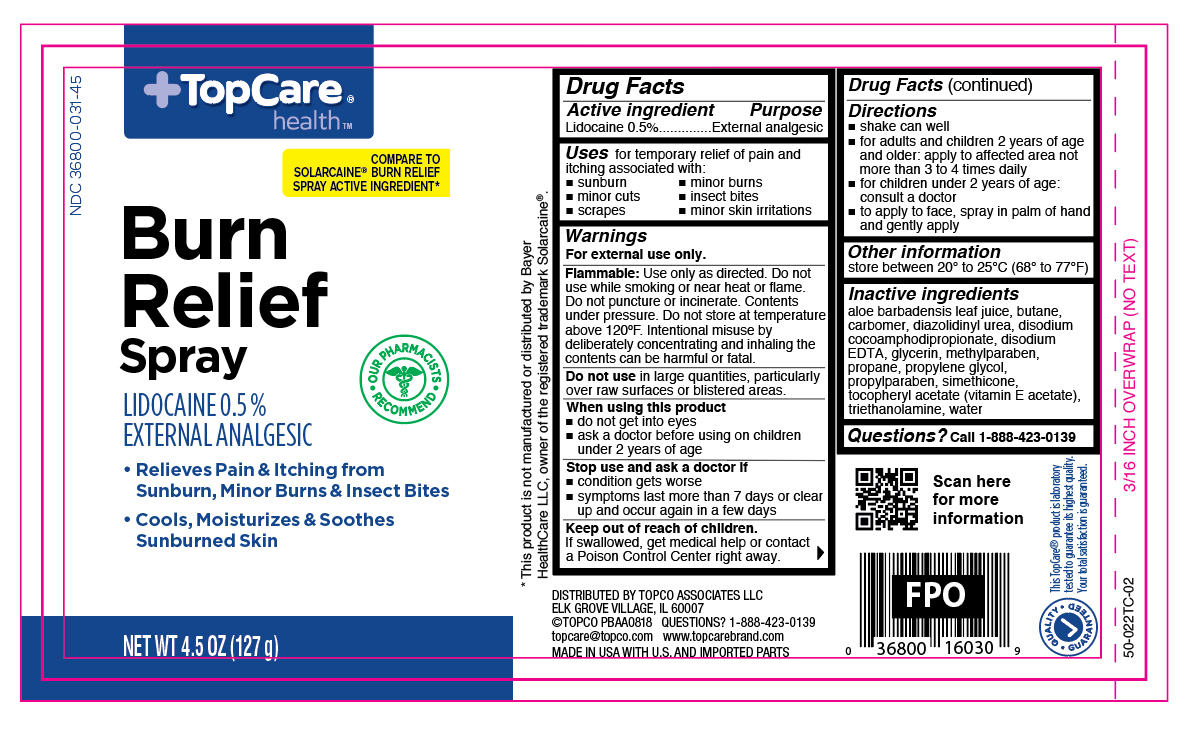 DRUG LABEL: Lidocaine
NDC: 36800-031 | Form: AEROSOL, SPRAY
Manufacturer: Topco Associates LLC
Category: otc | Type: HUMAN OTC DRUG LABEL
Date: 20251106

ACTIVE INGREDIENTS: LIDOCAINE 0.64 g/127 g
INACTIVE INGREDIENTS: ALOE VERA LEAF; BUTANE; CARBOMER 940; DIAZOLIDINYL UREA; DISODIUM COCOAMPHODIPROPIONATE; EDETATE DISODIUM; GLYCERIN; METHYLPARABEN; PROPANE; PROPYLENE GLYCOL; PROPYLPARABEN; .ALPHA.-TOCOPHEROL ACETATE; TROLAMINE; WATER

TopCare Burn Relief Spray

Active Ingredients

Lidocaine 0.5%

Purpose

External analgesic

Uses

for temporary relief of pain and itching associated with:

- sunburn
- minor burns
- minor cuts
- insect bites
- scrapes
- minor skin irritations

Warnings

For external use only.

Flammable:

Use only as directed. Do not use while smoking or near heat or flame. Do not puncture or incinerate. Contents under pressure. Do not store at temperature above 120ºF. Intentional misuse by deliberately concentrating and inhaling the contents can be harmful or fatal.

Do not use

in large quantities, particularly over raw surfaces or blistered areas.

When using this product

- do not get into eyes
- ask a doctor before using on children under 2 years of age

Stop use and ask a doctor if

- condition gets worse
- symptoms last more than 7 days or clear up and occur again in a few days

Keep out of reach of children.

If swallowed, get medical help or contact a Poison Control Center right away.

Directions

- shake can well
- for adults and children 2 years of age and older: apply to affected area not more than 3 to 4 times daily
- for children under 2 years of age: consult a doctor
- to apply to face, spray in palm of hand and gently apply

Other information

store between 20º and 25ºC (68º and 77ºF)

Inactive ingredients

aloe barbadensis leaf juice, butane, carbomer, diazolidinyl urea, disodium cocoamphodipropionate, disodium EDTA, glycerin, methylparaben, propane, propylene glycol, propylparaben, simethicone, tocopheryl acetate (vitamin E acetate), triethanolamine, water

Questions?

Call 1-888-423-0139

Principal Display Panel

Top Care health

Burn Relief Spray

LIDOCAINE 0.5%

EXTERNAL ANALGESIC

- Relieves Pain & Itching from Sunburn, Minor Burns & Insect Bites
- Cools, Moisturizes & Soothes Sunburned Skin

NET WT 4.5 OZ (127 g)